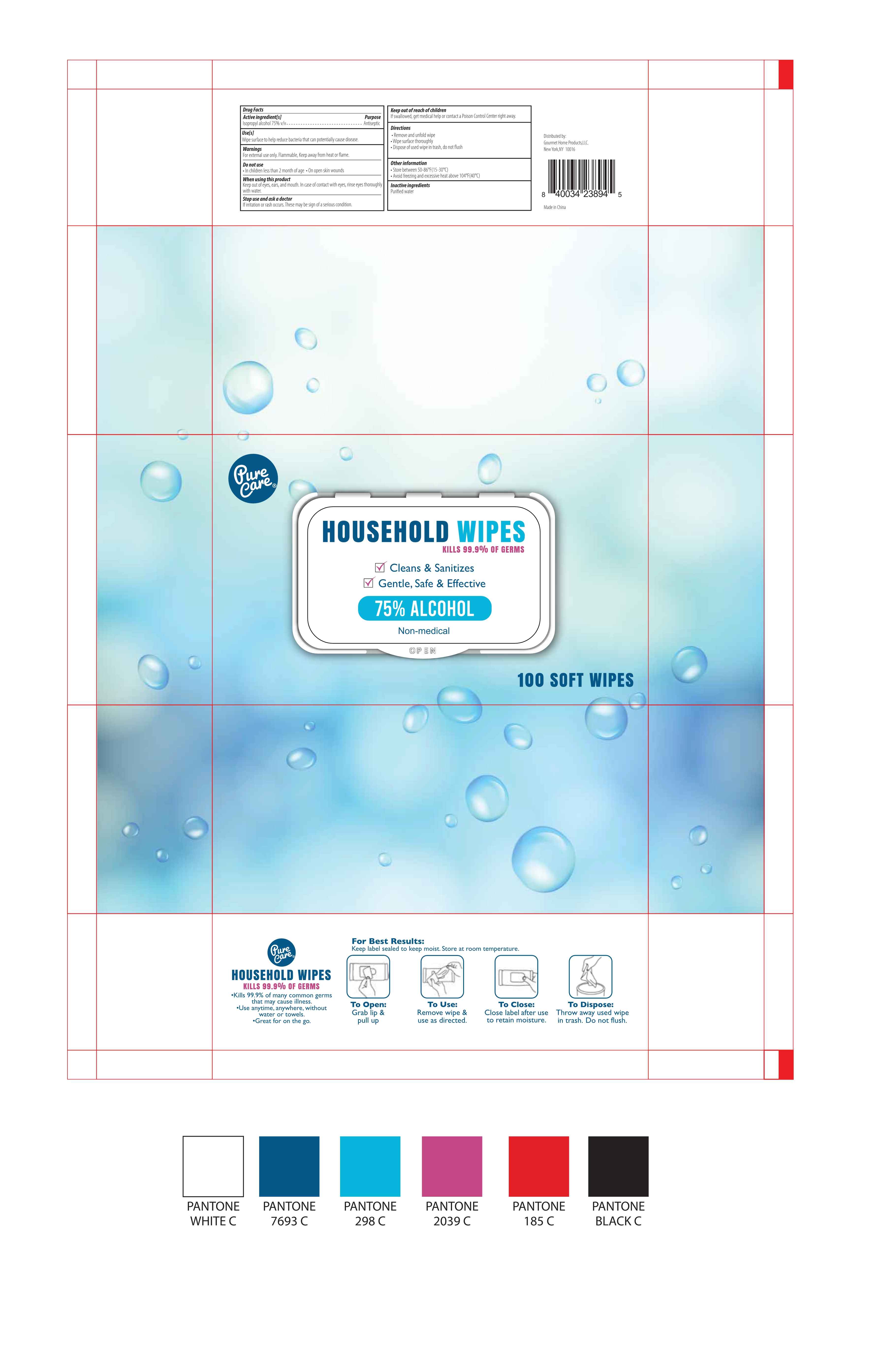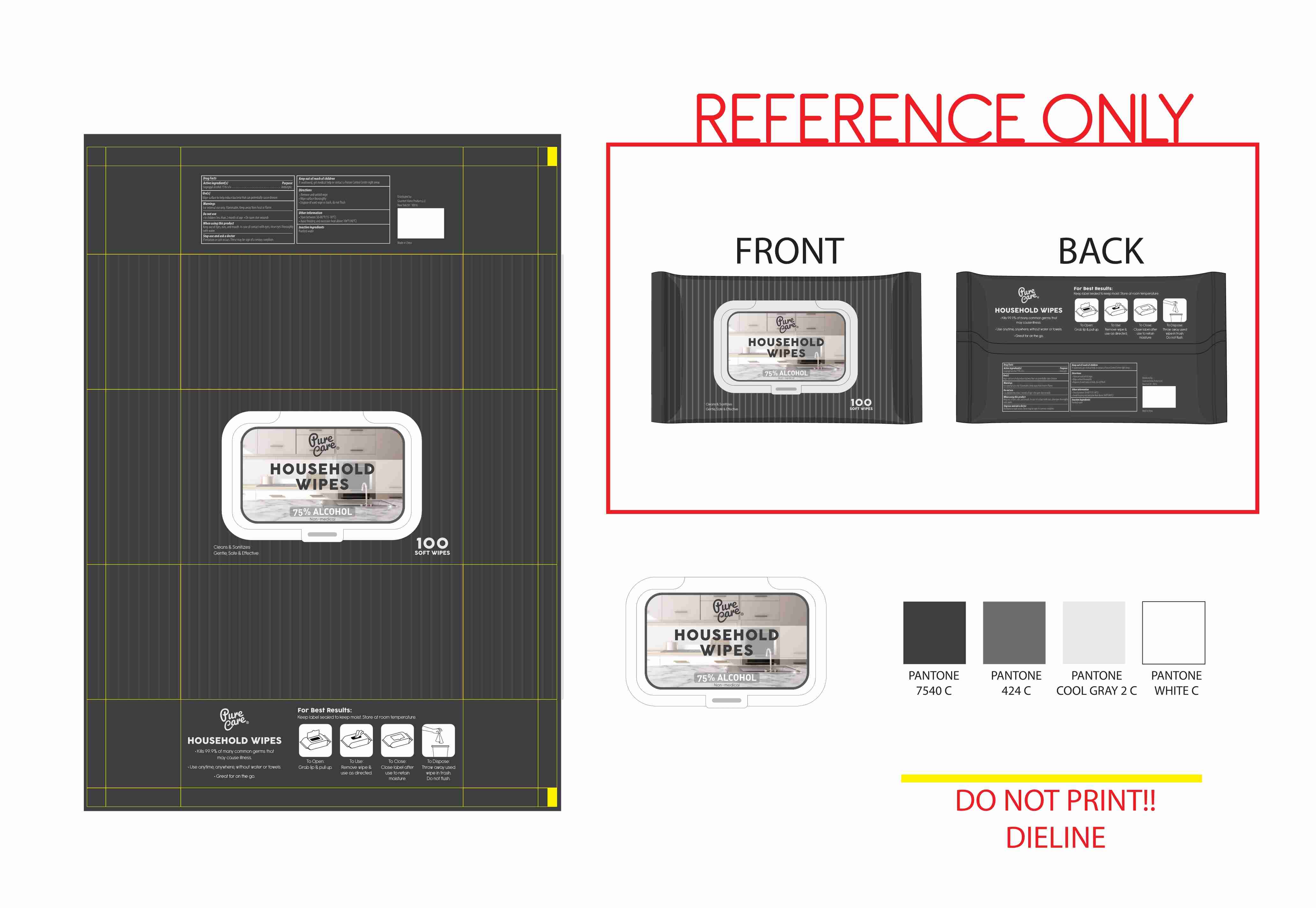 DRUG LABEL: PURE CARE -ALCOHOL WIPES
NDC: 54016-020 | Form: CLOTH
Manufacturer: Jinhua Huihuang Non-woven Products Co., Ltd.
Category: otc | Type: HUMAN OTC DRUG LABEL
Date: 20201210

ACTIVE INGREDIENTS: ISOPROPYL ALCOHOL 75 mL/100 mL
INACTIVE INGREDIENTS: WATER

PURE CARE -ALCOHOL WIPES
100pcs 54016-020-12

Active Ingredient(s)

Isopropyl alcohol 75% v/v

Purpose

Antiseptic

Use

Wipe surface to help reduce bacteria that can potentially cause disease.

Warnings

For external use only. Flammable, Keep away from heat or flame.

Do not use

- In children less than 2 month of age
- On open skin wounds

When using this product, Keep out of eyes, ears, and mouth. In case of contact with eyes, rinse eyes with water.

Stop use and ask a doctor if irritation or rash occurs. These may be sign of a serious condition.

Keep out of reach of children, If swallowed, get medical help or contact a Poison Control Center right away.

Directions

- Remove and unfold wipe
- Wipe surface thoroughly
- Dispose of used wipe in trash, do not flush

Other information

- Store between 50-86℉(15-30℃)
- Avoid freezing and excessive heat above 104℉(40℃)

Inactive ingredients

Purified water

Package Label - Principal Display Panel

100pcs NDC: 54016-020-12